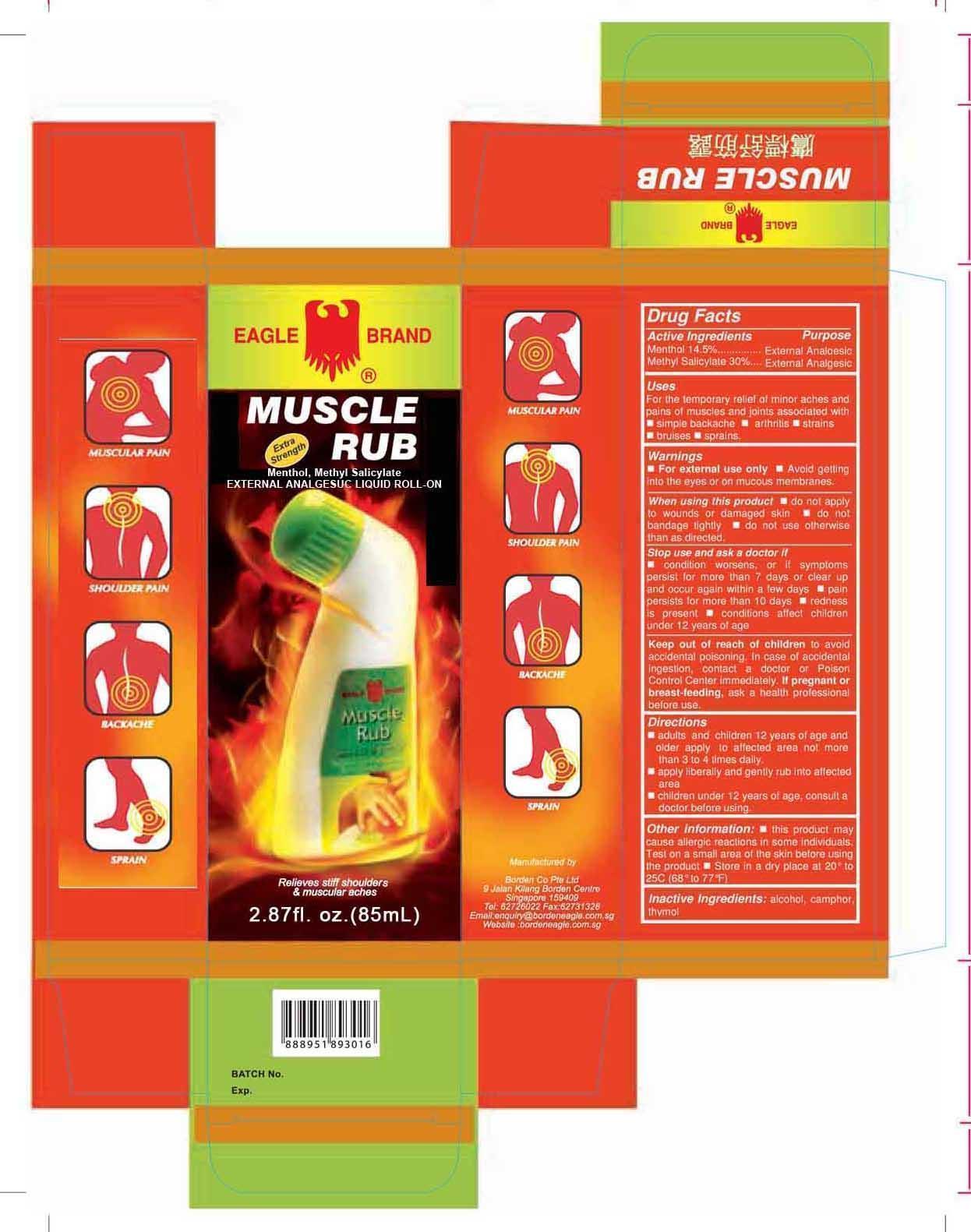 DRUG LABEL: Eagle
NDC: 43405-010 | Form: LIQUID
Manufacturer: Borden Company (Private) Limited
Category: otc | Type: HUMAN OTC DRUG LABEL
Date: 20241002

ACTIVE INGREDIENTS: MENTHOL 14.5 g/100 mL; METHYL SALICYLATE 30 g/100 mL
INACTIVE INGREDIENTS: ALCOHOL; CAMPHOR (SYNTHETIC); THYMOL

EgleMscleRubRllonMthnlMthylSlcte

Active Ingredients

Menthol 14.5%
Methyl Salicylate 30%

Purpose

External Analgesic

Uses

For the temporary relief of minor aches and pains of muscles and joint associated with ■ simple backache ■ arthritis ■ strains

■ bruises ■ sprains

Warnings

■ For external use only ■ Avoid getting into eyes and mucous membranes

When using this product

■ do not apply to wound or damaged skin ■ do not bandage tightly ■ do not use otherwise than as directed

Stop use and ask a doctor if

■ condition worsens, or if symptoms persist for more than 7 days or clear up and occur again within a few days ■ pain persists for more than 10 days ■ redness is present ■ conditions affect children under 12 years of age

Keep this drug out of reach of children

to avoid accidental poisoning. In case of accidental ingestion, contact a doctor or Poison Control Center immediately. If pregnant or breast-feeding, ask a health professional before use

Directions

■ adults and children 12 years of age and older apply to affected area not more than 3 to 4 time daily. ■ apply liberally and gently rub into affected area ■ children under 12 years of age, consult a doctor before using.

Inactive ingredients

alcohol, camphor, thymol